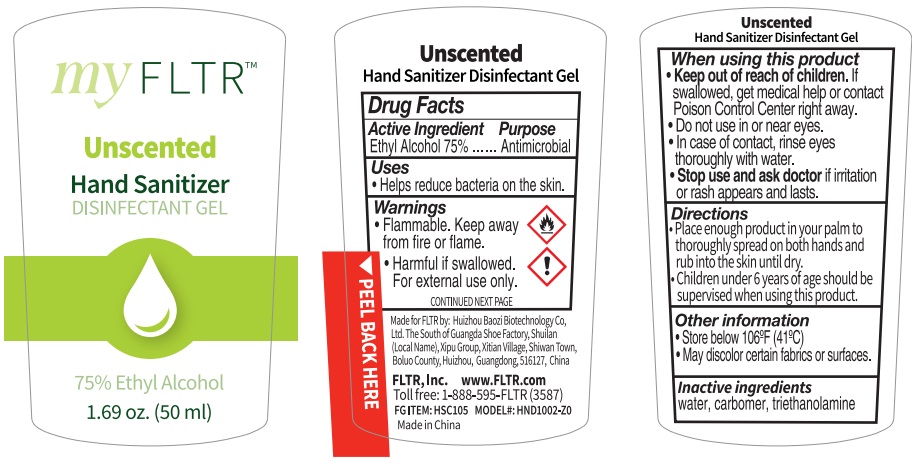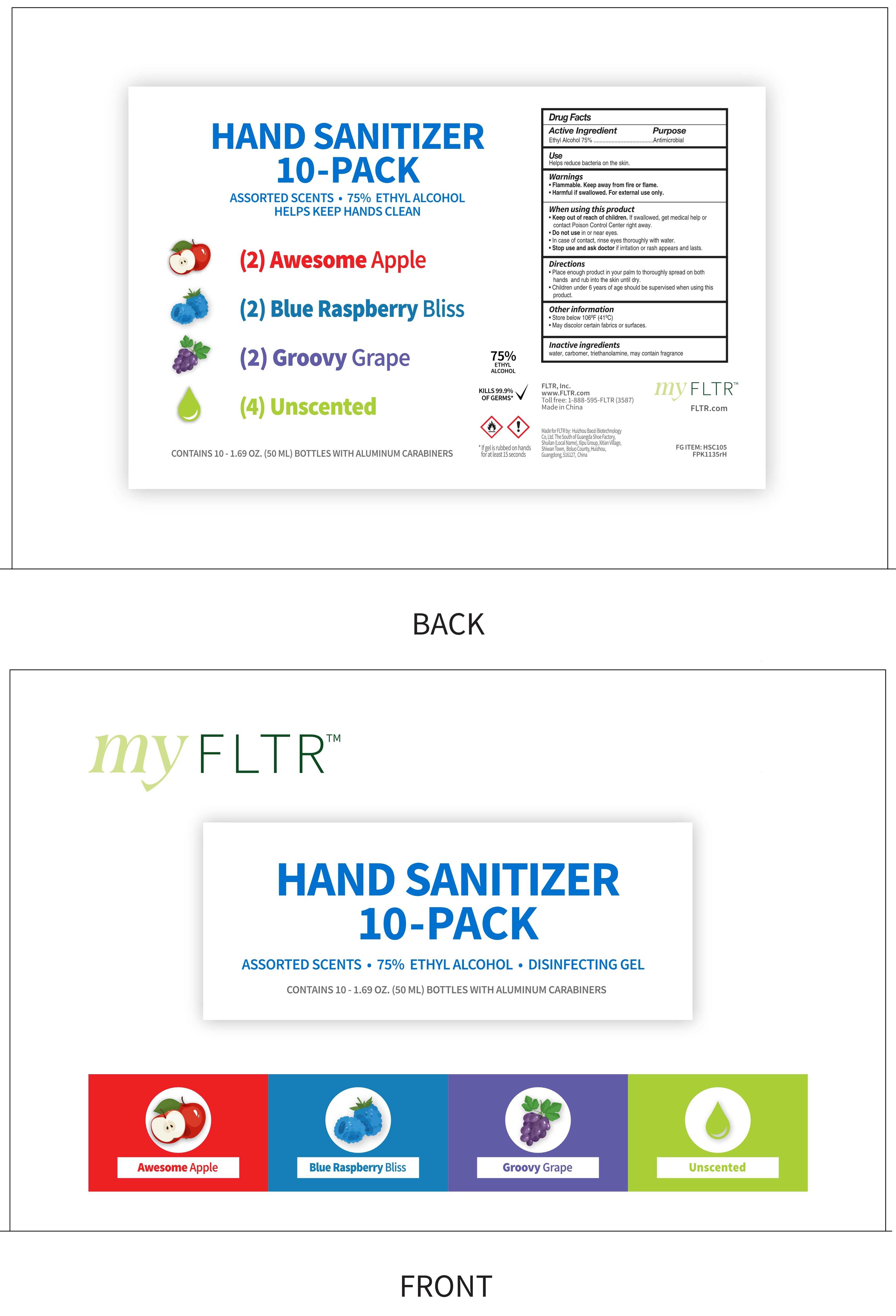 DRUG LABEL: Hand sanitizer
NDC: 74881-012 | Form: GEL
Manufacturer: Huizhou Baozi Biotechnology Co.,Ltd.
Category: otc | Type: HUMAN OTC DRUG LABEL
Date: 20201218

ACTIVE INGREDIENTS: ALCOHOL 75 mL/100 mL
INACTIVE INGREDIENTS: TROLAMINE; CARBOMER HOMOPOLYMER, UNSPECIFIED TYPE; WATER

74881-012
90081-008
Unscented Hand sanitizer

Active Ingredient

Eohyl Alcohol 75%

Purpose

Antimicrobial

Uses

Hand sanitizer to help reduce bacteria on skin

Do not use in or near eyes. In case of contact, rinse eyes thoroughly with water.

Warnings

Flammable. Keep away from fire or flame.
Harmful if swallowed.
For external use only.
CONTINUED NEXT PAGE

WHEN USING THIS PRODUCT

Keep out of reach of children . If swallowed, get medkal help or contact Poison Control Center right away.

Do not use in or near eyes. In case of contact, rinse eyes thoroughly with water.

Stop use and ask aoctor if irritatioin or rash appears and lasts.

Stop use and ask aoctor if irritatioin or rash appears and lasts.

Keep out of reach of children . If swallowed, get medkal help or contact Poison Control Center right away.

Directions

Directions: Place enough product in your palm to thoroughly spread on both hands and rub into the skin until dry

Children under 6 years of age should be supervised when using this product

Other information

Store below 106°F (41°C)
May discolor certain fabrics or suriaces.

Inactive ingredients

water, caroomer, triethanolamine

Package Label - Principal Display Panel

HSC105 Retail Pouch

74881-012-01